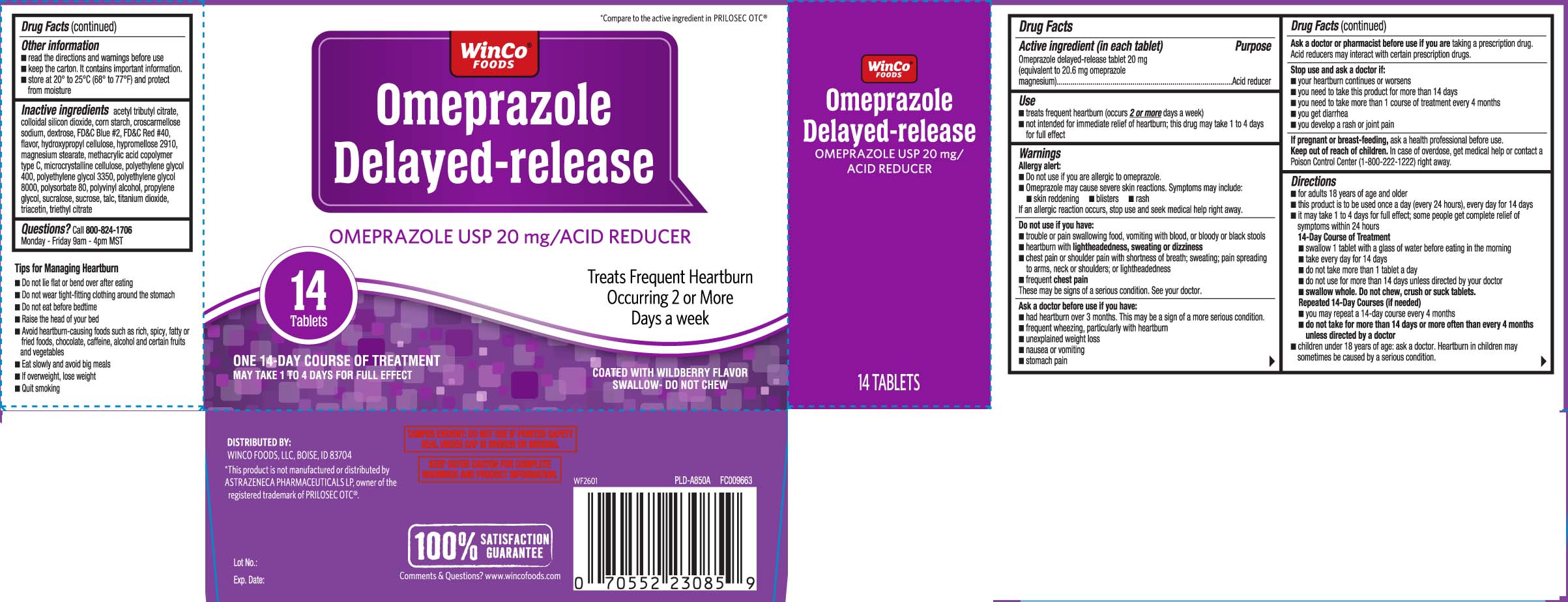 DRUG LABEL: Omeprazole
NDC: 67091-464 | Form: TABLET, DELAYED RELEASE
Manufacturer: WinCo Foods, LLC
Category: otc | Type: HUMAN OTC DRUG LABEL
Date: 20260114

ACTIVE INGREDIENTS: OMEPRAZOLE MAGNESIUM 20.6 mg/1 1
INACTIVE INGREDIENTS: ACETYLTRIBUTYL CITRATE; SILICON DIOXIDE; STARCH, CORN; CROSCARMELLOSE SODIUM; DEXTROSE; FD&C BLUE NO. 2; FD&C RED NO. 40; HYDROXYPROPYL CELLULOSE, UNSPECIFIED; HYPROMELLOSE 2910 (15 MPA.S); MAGNESIUM STEARATE; METHACRYLIC ACID AND ETHYL ACRYLATE COPOLYMER; POLYETHYLENE GLYCOL 400; POLYETHYLENE GLYCOL 3350; POLYETHYLENE GLYCOL 8000; POLYVINYL ALCOHOL, UNSPECIFIED; PROPYLENE GLYCOL; SUCROSE; TALC; TITANIUM DIOXIDE; TRIACETIN; TRIETHYL CITRATE; MICROCRYSTALLINE CELLULOSE; POLYSORBATE 80; SUCRALOSE

OMEPRAZOLE MAGNESIUM DELAYED-RELEASE TABLETS

Active ingredient (in each tablet)

Omeprazole delayed-release tablet 20 mg

(equivalent to 20.6 mg omeprazole magnesium)

Purpose

Acid reducer

Use

- treats frequent heartburn (occurs 2 or more days a week)
- not intended for immediate relief of heartburn; this drug may take 1 to 4 days for full effect

Warnings

Allergy alert:

- Do not use if you are allergic to omeprazole
- Omeprazole may cause severe skin reactions. Symptoms may include:
  - skin reddening
  - blisters
  - rash

if an allergic reaction occurs, stop use and seek medical help right away.

Do not use if you have:

- trouble or pain swallowing food, vomiting with blood, or bloody or black stools
- heartburn with lightheadedness, sweating or dizziness
- chest pain or shoulder pain with shortness of breath; sweating; pain spreading to arms, neck or shoulders; or lightheadedness
- frequent chest pain

These may be signs of a serious condition. See your doctor.

Ask a doctor before use if you have:

- had heartburn over 3 months. This may be a sign of a more serious condition.
- frequent wheezing, particularly with heartburn
- unexplained weight loss 
- nausea or vomiting
- stomach pain

Ask a doctor or pharmacist before use if you are

taking a prescription drug.

Acid reducers may interact with certain prescription drugs.

Stop use and ask a doctor if:

- your heartburn continues or worsens
- you need to take this product for more than 14 days
- you need to take more than 1 course of treatment every 4 months
- you get diarrhea
- you develop a rash or joint pain

If pregnant or breast-feeding,

ask a health professional before use.

Keep out of reach of children.

In case of overdose, get medical help or contact a Poison Control Center (1-800-222-1222) right away.

Directions

- for adults 18 years of age and older
- this product is to be used once a day (every 24 hours), every day for 14 days
- it may take 1 to 4 days for full effect; some people get complete relief of symptoms within 24 hours

14-Day Course of Treatment

- swallow 1 tablet with a glass of water before eating in the morning
- take everyday for 14 days
- do not take more than 1 tablet a day
- do not use for more than 14 days unless directed by your doctor
- swallow whole. Do not chew, crush or suck tablets.

Repeated 14-Day Courses (if needed)

- you may repeat a 14-day course every 4 months
- do not take for more than 14 days or more often than every 4 months unless directed by a doctor

- children under 18 years of age: ask a doctor. Heartburn in children may sometimes be caused by a serious condition.

Other information

- read the directions and warnings before use
- Keep the carton. It contains important information.
- store at 20° to 25°C (68° to 77°F) and protect from moisture

Inactive ingredients

acetyl tributyl citrate, colloidal silicon dioxide, corn starch, croscarmellose sodium, dextrose, FD&C Blue #2, FD&C Red #40, flavor, hydroxypropyl cellulose, hypromellose 2910, magnesium stearate, methacrylic acid copolymer type C, microcrystalline cellulose, polyethylene glycol 400, polyethylene glycol 3350, polyethylene glycol 8000, polysorbate 80, polyvinyl alcohol, propylene glycol, sucralose, sucrose, talc, titanium dioxide, triacetin, triethyl citrate

Tips for Managing Heartburn

- Do not lie flat or bend over after eating
- Do not wear tight-fitting clothing around the stomach
- Do not eat before bedtime
- Raise the head of your bed
- Avoid heartburn-causing foods such as rich, spicy, fatty or fried foods, chocolate, caffeine, alcohol and certain fruits and vegetables
- Eat slowly and avoid big meals
- If overweight, lose weight
- Quit smoking

Principal display panel

†Compare to the active ingredient in Prilosec® OTC

Omeprazole

Delayed-release

OMEPRAZOLE USP 20 mg ACID REDUCER

Treats Frequent heartburn

Occurring 2 or More Days a week

COATED WITH WILDBERRY FLAVOR

SWALLOW- DO NOT CHEW

Tablets

ONE 14-DAY COURSE OF TREATMENT

MAY TAKE 1 TO 4 DAYS FOR FULL EFFECT

*This product is not manufactured or distributed by ASTRAZENECA PHARMACEUTICALS LP, owner of the registered trademark of PRILOSEC OTC®.

TAMPER EVIDENT: DO NOT USE IF PRINTED SAFETY SEAL UNDER CAP IS BROKEN OR MISSING.

KEEP OUTER CARTON FOR COMPLETE WARNINGS AND PRODUCT INFORMATION.

DISTRIBUTED BY:

WINCO FOODS, LLC, BOISE, ID 83704

Package label

WINCO FOODS Acid Reducer Wildberry Flavor